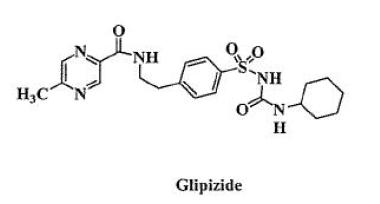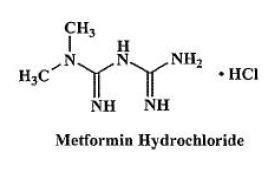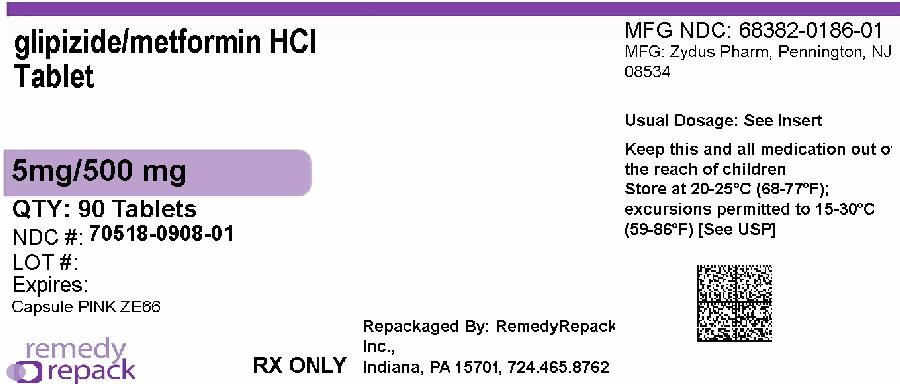 DRUG LABEL: Glipizide and Metformin Hydrochloride
NDC: 70518-0908 | Form: TABLET, FILM COATED
Manufacturer: REMEDYREPACK INC.
Category: prescription | Type: HUMAN PRESCRIPTION DRUG LABEL
Date: 20260212

ACTIVE INGREDIENTS: GLIPIZIDE 5 mg/1 1; METFORMIN HYDROCHLORIDE 500 mg/1 1
INACTIVE INGREDIENTS: POLYETHYLENE GLYCOL, UNSPECIFIED; POVIDONE; TITANIUM DIOXIDE; CELLULOSE, MICROCRYSTALLINE; CROSCARMELLOSE SODIUM; FERRIC OXIDE RED; HYPROMELLOSES; MAGNESIUM STEARATE

Glipizide and Metformin Hydrochloride Tablets, USP

DESCRIPTION

Glipizide and metformin hydrochloride tablets contain two oral antihyperglycemic drugs used in the management of type 2 diabetes, glipizide and metformin hydrochloride.

Glipizide is an oral antihyperglycemic drug of the sulfonylurea class. The chemical name for glipizide is 1-cyclohexyl-3-[[ p-[2-(5-methylpyrazinecarboxamido)ethyl]phenyl] sulfonyl]urea. Glipizide, USP is a white to almost white; crystalline powder with a molecular formula of C21H27N5O4S, a molecular weight of 445.55 and a pKaof 5.9. The structural formula is represented below.

Metformin hydrochloride, USP is an oral antihyperglycemic drug used in the management of type 2 diabetes. Metformin hydrochloride (N,N-dimethylimidodicarbonimidic diamide monohydrochloride) is not chemically or pharmacologically related to sulfonylureas, thiazolidinediones, or α-glucosidase inhibitors. It is white crystalline compound with a molecular formula of C4H12ClN5(monohydrochloride) and a molecular weight of 165.63. Metformin hydrochloride is freely soluble in water, slightly soluble in alcohol, practically insoluble in acetone and in methylene chloride. The pKaof metformin is 12.4. The pH of a 1% aqueous solution of metformin hydrochloride is 6.68. The structural formula is as shown:

Each glipizide and metformin hydrochloride tablet intended for oral administration contains glipizide, 2.5 mg or 5 mg and metformin hydrochloride, 250 mg or 500 mg. In addition, each tablet contains the following inactive ingredients: croscarmellose sodium, hydroxypropyl methylcellulose, magnesium stearate, microcrystalline cellulose, polyethylene glycol, povidone and titanium dioxide. Additionally each 2.5 mg/250 mg and 5 mg/500 mg tablet contains iron oxide red and each 2.5 mg/500 mg tablet contains polysorbate 80.

CLINICAL PHARMACOLOGY

Mechanism of Action:

Glipizide and metformin hydrochloride tablet combines glipizide and metformin hydrochloride, two antihyperglycemic agents with complementary mechanisms of action, to improve glycemic control in patients with type 2 diabetes.

Glipizide appears to lower blood glucose acutely by stimulating the release of insulin from the pancreas, an effect dependent upon functioning beta cells in the pancreatic islets. Extrapancreatic effects may play a part in the mechanism of action of oral sulfonylurea hypoglycemic drugs. The mechanism by which glipizide lowers blood glucose during long-term administration has not been clearly established. In man, stimulation of insulin secretion by glipizide in response to a meal is undoubtedly of major importance. Fasting insulin levels are not elevated even on long-term glipizide administration, but the post prandial insulin response continues to be enhanced after at least 6 months of treatment.

Metformin hydrochloride is an antihyperglycemic agent that improves glucose tolerance in patients with type 2 diabetes, lowering both basal and postprandial plasma glucose. Metformin hydrochloride decreases hepatic glucose production, decreases intestinal absorption of glucose, and improves insulin sensitivity by increasing peripheral glucose uptake and utilization.

Glipizide and Metformin Hydrochloride Tablets:

In a single dose study in healthy subjects, the glipizide and metformin components of glipizide and metformin hydrochloride tablets 5 mg/500 mg were bioequivalent to co-administered glipizide and metformin hydrochloride. Following administration of a single glipizide and metformin hydrochloride 5 mg/500 mg tablet in healthy subjects with either a 20% glucose solution or a 20% glucose solution with food, there was a small effect of food on peak plasma concentration (Cmax) and no effect of food on area under the curve (AUC) of the glipizide component. Time to peak plasma concentration (Tmax) for the glipizide component was delayed 1 hour with food relative to the same tablet strength administered fasting with a 20% glucose solution. Cmaxfor the metformin component was reduced approximately 14% by food whereas AUC was not affected. Tmaxfor the metformin component was delayed 1 hour after food.

Glipizide:

Gastrointestinal absorption of glipizide is uniform, rapid, and essentially complete. Peak plasma concentrations occur 1 to 3 hours after a single oral dose. Glipizide does not accumulate in plasma on repeated oral administration. Total absorption and disposition of an oral dose was unaffected by food in normal volunteers, but absorption was delayed by about 40 minutes.

Metformin Hydrochloride:

The absolute bioavailability of a 500 mg metformin hydrochloride tablet given under fasting conditions is approximately 50% to 60%. Studies using single oral doses of metformin tablets of 500 mg and 1500 mg, and 850 mg to 2550 mg, indicate that there is a lack of dose proportionality with increasing doses, which is due to decreased absorption rather than an alteration in elimination. Food decreases the extent of and slightly delays the absorption of metformin, as shown by approximately a 40% lower peak concentration and a 25% lower AUC in plasma and a 35-minute prolongation of time to peak plasma concentration following administration of a single 850 mg tablet of metformin with food, compared to the same tablet strength administered fasting. The clinical relevance of these decreases is unknown.

Glipizide:

Protein binding was studied in serum from volunteers who received either oral or intravenous glipizide and found to be 98% to 99% one hour after either route of administration. The apparent volume of distribution of glipizide after intravenous administration was 11 liters, indicative of localization within the extracellular fluid compartment. In mice, no glipizide or metabolites were detectable autoradiographically in the brain or spinal cord of males or females, nor in the fetuses of pregnant females. In another study, however, very small amounts of radioactivity were detected in the fetuses of rats given labeled drug.

Metformin Hydrochloride:

The apparent volume of distribution (V/F) of metformin following single oral doses of 850 mg averaged 654±358 L. Metformin is negligibly bound to plasma proteins. Metformin partitions into erythrocytes, most likely as a function of time. At usual clinical doses and dosing schedules of metformin, steady state plasma concentrations of metformin are reached within 24 to 48 hours and are generally <1 µg/mL. During controlled clinical trials, maximum metformin plasma levels did not exceed 5 µg/mL, even at maximum doses.

Glipizide:

The metabolism of glipizide is extensive and occurs mainly in the liver. The primary metabolites are inactive hydroxylation products and polar conjugates and are excreted mainly in the urine. Less than 10% unchanged glipizide is found in the urine. The half-life of elimination ranges from 2 to 4 hours in normal subjects, whether given intravenously or orally. The metabolic and excretory patterns are similar with the two routes of administration, indicating that first-pass metabolism is not significant.

Metformin Hydrochloride:

Intravenous single-dose studies in normal subjects demonstrate that metformin is excreted unchanged in the urine and does not undergo hepatic metabolism (no metabolites have been identified in humans) nor biliary excretion. Renal clearance (see Table 1) is approximately 3.5 times greater than creatinine clearance, which indicates that tubular secretion is the major route of metformin elimination. Following oral administration, approximately 90% of the absorbed drug is eliminated via the renal route within the first 24 hours, with a plasma elimination half-life of approximately 6.2 hours. In blood, the elimination half-life is approximately 17.6 hours, suggesting that the erythrocyte mass may be a compartment of distribution.

Patients with Type 2 Diabetes:

In the presence of normal renal function, there are no differences between single- or multiple-dose pharmacokinetics of metformin between patients with type 2 diabetes and normal subjects (see Table 1), nor is there any accumulation of metformin in either group at usual clinical doses.

Renal Impairment

The metabolism and excretion of glipizide may be slowed in patients with impaired renal

function (see CONTRAINDICATIONS, WARNINGS, PRECAUTIONS, and DOSAGE AND ADMINISTRATION).

In patients with decreased renal function, the plasma and blood half-life of metformin is prolonged and the renal clearance is decreased (see Table 1; also, see WARNINGS).

Hepatic Impairment

The metabolism and excretion of glipizide may be slowed in patients with impaired hepatic function (see PRECAUTIONS).

No pharmacokinetic studies have been conducted in patients with hepatic insufficiency for metformin.

Geriatrics:

There is no information on the pharmacokinetics of glipizide in elderly patients.

Limited data from controlled pharmacokinetic studies of metformin in healthy elderly subjects suggest that total plasma clearance is decreased, the half-life is prolonged, and Cmaxis increased, compared to healthy young subjects. From these data, it appears that the change in metformin pharmacokinetics with aging is primarily accounted for by a change in renal function (see Table 1).

Table 1 Select Mean (±S.D.) Metformin Pharmacokinetic Parameters Following Single or Multiple Oral Doses of Metformin
Subject Groups: Metformin Dose [All doses given fasting except the first 18 doses of the multiple-dose studies] (Number of Subjects) | Cmax [Peak plasma concentration] (µg/mL) | Tmax [Time to peak plasma concentration] (hrs) | Renal Clearnance (mL/min)
Healthy, Nondiabetic Adults:
500 mg SD [SD = single dose] (24) | 1.03 (±0.33) | 2.75 (±0.81) | 600 (±132)
850 mg SD (74) [Combined results (average means) of five studies: mean age 32 years (range 23 to 59 years)] | 1.60 (±0.38) | 2.64 (±0.42) | 552 (±139)
850 mg t.i.d. for 19 doses [Kinetic study done following dose 19, given fasting] (9) | 2.01(±0.42) | 1.79 (±0.94) | 642 (±173)
Adults with Type 2 Diabetes:
850 mg SD (23) | 1.48 (±0.5) | 3.32 (±1.08) | 491 (±138)
850 mg t.i.d. for 19 doses (9) | 1.90 (±0.62) | 2.01 (±1.22) | 550 (±160)
Elderly [Elderly subjects, mean age 71 years (range 65 to 81 years)] , Healthy Nondiabetic Adults:
850 mg SD (12) | 2.45 (±0.70) | 2.71 (±1.05) | 412 (±98)
Renal-impaired Adults: 850 mg SD
Mild (CLcr [CLcr= creatinine clearance normalized to body surface area of 1.73 m 2] 61 to 90 mL/min) (5) | 1.86 (±0.52) | 3.20 (±0.45) | 384 (±122)
Moderate (CLcr 31 to 60 mL/min) (4) | 4.12 (±1.83) | 3.75 (±0.50) | 108 (±57)
Severe (CLcr 10 to 30 mL/min) (6) | 3.93 (±0.92) | 4.01 (±1.10) | 130 (±90)

Pediatrics:

No data from pharmacokinetic studies in pediatric subjects are available for glipizide. After administration of a single oral metformin hydrochloride 500 mg tablet with food, geometric mean metformin Cmaxand AUC differed less than 5% between pediatric type 2 diabetic patients (12 to 16 years of age) and gender- and weight-matched healthy adults (20 to 45 years of age), all with normal renal function.

Gender:

There is no information on the effect of gender on the pharmacokinetics of glipizide.

Metformin pharmacokinetic parameters did not differ significantly in subjects with or without type 2 diabetes when analyzed according to gender (males=19, females=16). Similarly, in controlled clinical studies in patients with type 2 diabetes, the antihyperglycemic effect of metformin was comparable in males and females.

Race:

No information is available on race differences in the pharmacokinetics of glipizide.

No studies of metformin pharmacokinetic parameters according to race have been performed. In controlled clinical studies of metformin in patients with type 2 diabetes, the antihyperglycemic effect was comparable in whites (n=249), blacks (n=51), and Hispanics (n=24).

Patients with Inadequate Glycemic Control on Diet and Exercise Alone:

In a 24-week, double-blind, active-controlled, multicenter international clinical trial, patients with type 2 diabetes, whose hyperglycemia was not adequately controlled with diet and exercise alone (hemoglobin A1c[HbA1c]>7.5% and ≤12% and fasting plasma glucose [FPG]<300 mg/dL) were randomized to receive initial therapy with glipizide 5 mg, metformin 500 mg, glipizide and metformin hydrochloride tablets 2.5 mg/250 mg, or glipizide and metformin hydrochloride tablets 2.5 mg/500 mg. After two weeks, the dose was progressively increased (up to the 12-week visit) to a maximum of four tablets daily in divided doses as needed to reach a target mean daily glucose (MDG) of ≤130 mg/dL. Trial data at 24 weeks are summarized in Table 2.

Table 2 Active-Controlled Trial of Glipizide and Metformin Hydrochloride Tablets as Initial Therapy: Summary of Trial Data at 24 Weeks
 | Glipizide Tablets 5 mg | Metformin Tablets 500 mg | Glipizide and Metformin Hydrochloride Tablets 2.5 mg/250 mg | Glipizide and Metformin Hydrochloride Tablets 2.5 mg/500 mg
Mean Final Dose | 16.7 mg | 1749 mg | 7.9 mg/791 mg | 7.4 mg/1477 mg
Hemoglobin A1c (%) | N=168 | N=171 | N=166 | N=163
Baseline Mean | 9.17 | 9.15 | 9.06 | 9.10
Final Mean | 7.36 | 7.47 | 6.93 | 6.95
Adjusted Mean Change from Baseline | -1.77 | -1.46 | -2.15 | -2.14
Different from Glipizide |  |  | -0.38 [p <0.001] | -0.37
Different from Metformin |  |  | -0.70 | -0.69
% Patients with Final HbA1c<7% | 43.5% | 35.1% | 59.6% | 57.1%
Fasting Plasma Glucose (mg/dL) | N=169 | N=176 | N=170 | N=169
Baseline Mean | 210.7 | 207.4 | 206.8 | 203.1
Final Mean | 162.1 | 163.8 | 152.1 | 148.7
Adjusted Mean Change from Baseline | -46.2 | -42.9 | -54.2 | -56.5
Different from Glipizide |  |  | -8.0 | -10.4
Different from Metformin |  |  | -11.3 | -13.6

After 24 weeks, treatment with glipizide and metformin hydrochloride tablets 2.5 mg/250 mg and 2.5 mg/500 mg resulted in significantly greater reduction in HbA1ccompared to glipizide and to metformin therapy. Also, glipizide and metformin hydrochloride tablets 2.5 mg/250 mg therapy resulted in significant reductions in FPG versus metformin therapy.

Increases above fasting glucose and insulin levels were determined at baseline and final study visits by measurement of plasma glucose and insulin for three hours following a standard mixed liquid meal. Treatment with glipizide and metformin hydrochloride tablets lowered the three-hour postprandial glucose AUC, compared to baseline, to a significantly greater extent than did the glipizide and the metformin therapies. Compared to baseline, glipizide and metformin hydrochloride tablets enhanced the postprandial insulin response, but did not significantly affect fasting insulin levels.

There were no clinically meaningful differences in changes from baseline for all lipid parameters between glipizide and metformin hydrochloride tablets therapy and either metformin therapy or glipizide therapy. The adjusted mean changes from baseline in body weight were: glipizide and metformin hydrochloride tablets 2.5 mg/250 mg, -0.4 kg; glipizide and metformin hydrochloride tablets 2.5 mg/500 mg, -0.5 kg; glipizide, -0.2 kg; and metformin, -1.9 kg. Weight loss was greater with metformin than with glipizide and metformin hydrochloride tablets.

Patients with Inadequate Glycemic Control on Sulfonylurea Monotherapy:

In an 18-week, double-blind, active-controlled U.S. clinical trial, a total of 247 patients with type 2 diabetes not adequately controlled (HbA1c≥ 7.5% and ≤ 12% and FPG < 300 mg/dL) while being treated with at least one-half the maximum labeled dose of a sulfonylurea (e.g., glyburide 10 mg, glipizide 20 mg) were randomized to receive glipizide (fixed dose, 30 mg), metformin (500 mg), or glipizide and metformin hydrochloride tablets 5 mg/500 mg. The doses of metformin and glipizide and metformin hydrochloride tablets were titrated (up to the eight-week visit) to a maximum of four tablets daily as needed to achieve MDG ≤ 130 mg/dL. Trial data at 18 weeks are summarized in Table 3.

Table 3 Glipizide and Metformin Hydrochloride Tablets as Second-Line Therapy: Summary of Trial Data at 18 Weeks
 | Glipizide Tablets 5 mg | Metformin Tablets 500 mg | Glipizide and Metformin Hydrochloride Tablets 5 mg/500 mg
Mean Final Dose | 30.0 mg | 1927 mg | 17.5 mg/1747 mg
Hemoglobin A1c (%) | N=79 | N=71 | N=80
Baseline Mean | 8.87 | 8.61 | 8.66
Final Adjusted Mean | 8.45 | 8.36 | 7.39
Different from Glipizide |  |  | -1.06 [p <0.001]
Different from Metformin |  |  | -0.98
% Patients with Final HbA1c<7% | 8.9% | 9.9% | 36.3%
Fasting Plasma Glucose (mg/dL) | N=82 | N=75 | N=81
Baseline Mean | 203.6 | 191.3 | 194.3
Adjusted Mean Change from Baseline | 7.0 | 6.7 | -30.4
Difference from Glipizide |  |  | -37.4
Different from Metformin |  |  | -37.2

After 18 weeks, treatment with glipizide and metformin hydrochloride tablets at doses up to 20 mg/2000 mg per day resulted in significantly lower mean final HbA1cand significantly greater mean reductions in FPG compared to glipizide and to metformin therapy. Treatment with glipizide and metformin hydrochloride tablets lowered the three-hour postprandial glucose AUC, compared to baseline, to a significantly greater extent than did the glipizide and the metformin therapies. Glipizide and metformin hydrochloride tablets did not significantly affect fasting insulin levels.

There were no clinically meaningful differences in changes from baseline for all lipid parameters between glipizide and metformin hydrochloride tablets therapy and either metformin therapy or glipizide therapy. The adjusted mean changes from baseline in body weight were: glipizide and metformin hydrochloride tablets 5 mg/500 mg, -0.3 kg; glipizide, -0.4 kg; and metformin, -2.7 kg. Weight loss was greater with metformin than with glipizide and metformin hydrochloride tablets.

INDICATIONS AND USAGE

Glipizide and metformin hydrochloride tablets are indicated as an adjunct to diet and exercise to improve glycemic control in adults with type 2 diabetes mellitus.

CONTRAINDICATIONS

Glipizide and metformin hydrochloride tablets are contraindicated in patients with:

1. Severe renal impairment (eGFR below 30 mlL/min/1.73 m^2)
2. Known hypersensitivity to glipizide or metformin hydrochloride.
3. Acute or chronic metabolic acidosis, including diabetic ketoacidosis, with or without coma. Diabetic ketoacidosis should be treated with insulin.

WARNINGS

WARNING: LACTIC ACIDOSIS

Post-marketing cases of metformin-associated lactic acidosis have resulted in death,hypothermia, hypotension, and resistant bradyarrhythmias. The onset of metformin-associated lactic acidosis is often subtle, accompanied only by nonspecific symptoms such as malaise, myalgias, respiratory distress, somnolence, and abdominal pain. Metformin-associated lactic acidosis was characterized by elevated blood lactate levels (> 5 mmol/Liter), anion gap acidosis (without evidence of ketonuria or ketonemia), an increased lactate/pyruvate ratio; and metformin plasma levels generally > 5 mcg/mL [see PRECAUTIONS] Risk factors for metformin-associated lactic acidosis include renal impairment, concomitant use of certain drugs (e.g., carbonic anhydrase inhibitors such as topiramate), age 65 years old or greater, having a radiological study with contrast, surgery and other procedures, hypoxic states (e.g., acute congestive heart failure), excessive alcohol intake, and hepatic impairment. Steps to reduce the risk of and manage metformin-associated lactic acidosis in these high risk groups are provided [see PRECAUTIONS].

If metformin-associated lactic acidosis is suspected, immediately discontinue glipizide and metformin hydrochloride and institute general supportive measures in a hospital setting.

Prompt hemodialysis is recommended [see PRECAUTIONS].

SPECIAL WARNING ON INCREASED RISK OF CARDIOVASCULAR MORTALITY

The administration of oral hypoglycemic drugs has been reported to be associated with increased cardiovascular mortality as compared to treatment with diet alone or diet plus insulin. This warning is based on the study conducted by the University Group Diabetes Program (UGDP), a long-term prospective clinical trial designed to evaluate the effectiveness of glucose-lowering drugs in preventing or delaying vascular complications in patients with non-insulin-dependent diabetes. The study involved 823 patients who were randomly assigned to one of four treatment groups (Diabetes 19 (Suppl. 2):747-830, 1970).

UGDP reported that patients treated for 5 to 8 years with diet plus a fixed dose of tolbutamide (1.5 grams per day) had a rate of cardiovascular mortality approximately 2½ times that of patients treated with diet alone. A significant increase in total mortality was not observed, but the use of tolbutamide was discontinued based on the increase in cardiovascular mortality, thus limiting the opportunity for the study to show an increase in overall mortality. Despite controversy regarding the interpretation of these results, the findings of the UGDP study provide an adequate basis for this warning. The patient should be informed of the potential risks and benefits of glipizide and of alternative modes of therapy.

Although only one drug in the sulfonylurea class (tolbutamide) was included in this study, it is prudent from a safety standpoint to consider that this warning may also apply to other hypoglycemic drugs in this class, in view of their close similarities in mode of action and chemical structure.

PRECAUTIONS

Glipizide-Metformin Hydrochloride Tablets:

Lactic Acidosis—There have been post-marketing cases of metformin-associated lactic acidosis, including fatal cases. These cases had a subtle onset and were accompanied by nonspecific symptoms such as malaise, myalgias, abdominal pain, respiratory distress, or increased somnolence; however, hypotension and resistant bradyarrhythmias have occurred with severe acidosis. Metformin-associated lactic acidosis was characterized by elevated blood lactate concentrations (> 5 mmol/L), anion gap acidosis (without evidence of ketonuria or ketonemia), and an increases lactate:pyruvate ratio; metformin plasma levels were generally > 5 mcg/mL. Metformin decreases liver uptake of lactate increasing lactate blood levels which may increase the risk of lactic acidosis, especially in patients at risk.

If metformin-associated lactic acidosis is suspected, general supportive measures should be instituted promptly in a hospital setting, along with immediate discontinuation of glipizide and metformin hydrochloride. In glipizide and metformin hydrochloride treated patients with a diagnosis or strong suspicion of lactic acidosis, prompt hemodialysis is recommended to correct the acidosis and remove accumulated metformin (metformin hydrochloride is dialyzable with a clearance of up to 170 mL/min under good hemodynamic conditions). Hemodialysis has often resulted in reversal of symptoms and recovery.

Educate patients and their families about the symptoms of lactic acidosis and if these symptoms occur instruct them to discontinue glipizide and metformin hydrochloride and report these symptoms to their healthcare provider.

For each of the known and possible risk factors for metformin-associated lactic acidosis,recommendations to reduce the risk of and manage metformin-associated lactic acidosis are provided below:

- Renal Impairment—The postmarketing metformin-associated lactic acidosis cases primarily occurred in patients with significant renal impairment. The risk of metformin accumulation and metformin-associated lactic acidosis increases with the severity of renal impairment because metformin is substantially excreted by the kidney Clinical recommendations based upon the patients renal function include (see Dosage and Administration, Clinical Pharmacology):
- Before initiating glipizide and metformin hydrochloride, obtain an estimated glomerular filtration rate (eGFR)
- Glipizide and metformin hydrochloride is contraindicated in patients with an eGFR less than 30 mL/min/1.73 m^2. Initiation of glipizide and metformin hydrochloride is not recommended in patients with eGFR between 30-45 mL/min/1.73 m^2(see Contraindications)
- Obtain an eGFR at least annually in all patients taking glipizide and metformin hydrochloride. In patients at risk for the development of renal impairment (e.g., the elderly), renal function should be assessed more frequently.
- In patients taking glipizide and metformin hydrochloride whose eGFR falls below 45 mL/min/1.73 m^2, assess the benefit and risk of continuing therapy.

- Drug interactions—The concomitant use of glipizide and metformin hydrochloride with specific drugs may increase the risk of metformin-associated lactic acidosis: those that impair renal function, result in significant hemodynamic change, interfere with acid-base balance, or increase metformin accumulation. Consider more frequent monitoring of patients.
- Age 65 or Greater—The risk of metformin-associated lactic acidosis increases with the patient's age because elderly patients have a greater likelihood of having hepatic, renal, or cardiac impairment than younger patients. Assess renal function more frequently in elderly patients.
- Radiologic studies with contrast—Administration of intravascular iodinated contrast agents in metformin-treated patients has led to an acute decrease in renal function and the occurrence of lactic acidosis. Stop glipizide and metformin hydrochloride at the time of, or prior to, an iodinated contrast imaging procedure in patients with an eGFR between 30 and 60 mlL/min/1.73 m^2; in patients with a history of hepatic impairment, alcoholism or heart failure, or in patients who will be administered intra-arterial iodinated contrast. Reevaluate eGFR 48 hours after the imaging procedure, and restart glipizide and metformin hydrochloride if renal function is stable.
- Hypoxic states—Several of the postmarketing cases of metformin-associated lactic acidosis occurred in the setting of acute congestive heart failure (particularly when accompanied by hypoperfusion and hypoxemia). Cardiovascular collapse (shock), acute myocardial infarction, sepsis, and other conditions associated with hypoxemia have been associated with lactic acidosis and may cause prerenal azotemia. When such an event occurs, discontinue glipizide and metformin hydrochloride.
- Excessive Alcohol intake—Alcohol is known to potentiate the effect of metformin on lactate metabolism. Patients, therefore, should be warned against excessive alcohol intake, acute or chronic, while receiving glipizide and metformin hydrochloride.
- Hepatic impairment—Patients with hepatic impairment have developed cases of metformin-associated lactic acidosis. This may be due to impaired lactate clearance resulting in higher lactate blood levels. Therefore, avoid use of glipizide and metformin hydrochloride in patients with clinical or laboratory evidence of hepatic disease.

Hypoglycemia:

Glipizide-metformin hydrochloride tablets are capable of producing hypoglycemia; therefore, proper patient selection, dosing, and instructions are important to avoid potential hypoglycemic episodes. The risk of hypoglycemia is increased when caloric intake is deficient, when strenuous exercise is not compensated by caloric supplementation, or during concomitant use with other glucose-lowering agents or ethanol. Renal insufficiency may cause elevated drug levels of both glipizide and metformin hydrochloride. Hepatic insufficiency may increase drug levels of glipizide and may also diminish gluconeogenic capacity, both of which increase the risk of hypoglycemic reactions. Elderly, debilitated, or malnourished patients and those with adrenal or pituitary insufficiency or alcohol intoxication are particularly susceptible to hypoglycemic effects. Hypoglycemia may be difficult to recognize in the elderly, and in people who are taking beta-adrenergic blocking drugs.

Renal and Hepatic Disease:

The metabolism and excretion of glipizide may be slowed in patients with impaired renal and/or hepatic function. If hypoglycemia should occur in such patients, it may be prolonged and appropriate management should be instituted.

Hemolytic Anemia:

Treatment of patients with glucose 6-phosphate dehydrogenase (G6PD) deficiency with sulfonylurea agents can lead to hemolytic anemia. Because glipizide and metformin hydrochloride tablets belong to the class of sulfonylurea agents, caution should be used in patients with G6PD deficiency and a non-sulfonylurea alternative should be considered.In postmarketing reports, hemolytic anemia has also been reported in patients who did not have known G6PD deficiency.

Vitamin B12 Levels:

In controlled clinical trials with metformin of 29 weeks duration, a decrease to subnormal levels of previously normal serum vitamin B12, without clinical manifestations, was observed in approximately 7% of patients. Such decrease, possibly due to interference with B12absorption from the B12-intrinsic factor complex, is, however, very rarely associated with anemia and appears to be rapidly reversible with discontinuation of metformin or vitamin B12supplementation. Measurement of hematologic parameters on an annual basis is advised in patients on metformin and any apparent abnormalities should be appropriately investigated and managed (see PRECAUTIONS: Laboratory Tests).

Certain individuals (those with inadequate vitamin B12or calcium intake or absorption) appear to be predisposed to developing subnormal vitamin B12levels. In these patients, routine serum vitamin B12measurements at two- to three-year intervals may be useful.

Macrovascular Outcomes

There have been no clinical studies establishing conclusive evidence of macrovascular risk reduction with glipizide and metformin hydrochloride or any other antidiabetic drug.

Glipizide and Metformin Hydrochloride Tablets:

Patients should be informed of the potential risks and benefits of glipizide and metformin hydrochloride tablets and of alternative modes of therapy. They should also be informed about the importance of adherence to dietary instructions, of a regular exercise program, and of regular testing of blood glucose, glycosylated hemoglobin, renal function, and hematologic parameters.

The risks of lactic acidosis associated with metformin therapy, its symptoms, and conditions that predispose to its development, as noted in the WARNINGSand PRECAUTIONSsections, should be explained to patients. Patients should be advised to discontinue glipizide and metformin hydrochloride tablets immediately and to promptly notify their health practitioner if unexplained hyperventilation, myalgia, malaise, unusual somnolence, or other nonspecific symptoms occur. Once a patient is stabilized on any dose level of glipizide and metformin hydrochloride tablets, gastrointestinal symptoms, which are common during initiation of metformin therapy, are unlikely to be drug related. Later occurrence of gastrointestinal symptoms could be due to lactic acidosis or other serious disease.

The risks of hypoglycemia, its symptoms and treatment, and conditions that predispose to its development should be explained to patients and responsible family members.

Patients should be counseled against excessive alcohol intake, either acute or chronic, while receiving glipizide and metformin hydrochloride tablets (see Patient Information Leafletprinted below).

Laboratory Tests:

Periodic fasting blood glucose and glycosylated hemoglobin (HbA1c) measurements should be performed to monitor therapeutic response.

Initial and periodic monitoring of hematologic parameters (e.g., hemoglobin/hematocrit and red blood cell indices) and renal function (serum creatinine) should be performed, at least on an annual basis. While megaloblastic anemia has rarely been seen with metformin therapy, if this is suspected, vitamin B12deficiency should be excluded.

Instruct patients to inform their doctor that they are taking glipizide and metformin hydrochloride tablets prior to any surgical or radiological procedure, as temporary discontinuation of glipizide and metformin hydrochloride tablets may be required until renal function has been confirmed to be normal (see Precautions).

Glipizide and Metformin Hydrochloride Tablets:

Certain drugs tend to produce hyperglycemia and may lead to loss of blood glucose control. These drugs include the thiazides and other diuretics, corticosteroids, phenothiazines, thyroid products, estrogens, oral contraceptives, phenytoin, nicotinic acid, sympathomimetics, calcium channel blocking drugs, and isoniazid. When such drugs are administered to a patient receiving glipizide and metformin hydrochloride tablets, the patient should be closely observed for loss of blood glucose control. When such drugs are withdrawn from a patient receiving glipizide and metformin hydrochloride tablets, the patient should be observed closely for hypoglycemia. Metformin is negligibly bound to plasma proteins and is, therefore, less likely to interact with highly protein-bound drugs such as salicylates, sulfonamides, chloramphenicol, and probenecid as compared to sulfonylureas, which are extensively bound to serum proteins.

Glipizide:

The hypoglycemic action of sulfonylureas may be potentiated by certain drugs including nonsteroidal anti-inflammatory agents, some azoles, and other drugs that are highly protein bound, salicylates, sulfonamides, chloramphenicol, probenecid, coumarins, monoamine oxidase inhibitors, and beta-adrenergic blocking agents. When such drugs are administered to a patient receiving glipizide and metformin hydrochloride tablets, the patient should be observed closely for hypoglycemia. When such drugs are withdrawn from a patient receiving glipizide and metformin hydrochloride tablets, the patient should be observed closely for loss of blood glucose control. In vitrobinding studies with human serum proteins indicate that glipizide binds differently than tolbutamide and does not interact with salicylate or dicumarol. However, caution must be exercised in extrapolating these findings to the clinical situation and in the use of glipizide and metformin hydrochloride tablets with these drugs.

A potential interaction between oral miconazole and oral hypoglycemic agents leading to severe hypoglycemia has been reported. Whether this interaction also occurs with the intravenous, topical, or vaginal preparations of miconazole is not known. The effect of concomitant administration of fluconazole and glipizide has been demonstrated in a placebo-controlled crossover study in normal volunteers. All subjects received glipizide alone and following treatment with 100 mg of fluconazole as a single oral daily dose for 7 days, the mean percent increase in the glipizide AUC after fluconazole administration was 56.9% (range: 35% to 81%).

In studies assessing the effect of colesevelam on the pharmacokinetics of glipizide ER in healthy volunteers, reductions in glipizide AUC0-∞and Cmaxof 12% and 13%, respectively, were observed when colesevelam was coadministered with glipizide ER. When glipizide ER was administered 4 hours prior to colesevelam, there was no significant change in glipizide AUC0-∞or Cmax, –4% and 0%, respectively. Therefore, glipizide and metformin hydrochloride tablets should be administered at least 4 hours prior to colesevelam to ensure that colesevelam does not reduce the absorption of glipizide.

Furosemide:

A single-dose, metformin-furosemide drug interaction study in healthy subjects demonstrated that pharmacokinetic parameters of both compounds were affected by co-administration. Furosemide increased the metformin plasma and blood Cmaxby 22% and blood AUC by 15%, without any significant change in metformin renal clearance. When administered with metformin, the Cmaxand AUC of furosemide were 31% and 12% smaller, respectively, than when administered alone, and the terminal half-life was decreased by 32%, without any significant change in furosemide renal clearance. No information is available about the interaction of metformin and furosemide when co-administered chronically.

Nifedipine:

A single-dose, metformin-nifedipine drug interaction study in normal healthy volunteers demonstrated that co-administration of nifedipine increased plasma metformin Cmaxand AUC by 20% and 9%, respectively, and increased the amount excreted in the urine. Tmaxand half-life were unaffected. Nifedipine appears to enhance the absorption of metformin. Metformin had minimal effects on nifedipine.

Drugs that reduce metformin clearance

Concomitant use of drugs that interfere with common renal tubular transport systems involved in the renal elimination of metformin (e.g., organic cationic transporter-2 [OCT2] / multidrug and toxin extrusion [MATE] inhibitors such as ranolazine, vandetanib, dolutegravir, and cimetidine) could increase systemic exposure to metformin and may increase the risk for lactic acidosis. Consider the benefits and risks of concomitant use. Such interaction between metformin and oral cimetidine has been observed in normal healthy volunteers in both single- and multiple-dose, metformin-cimetidine drug interaction studies, with a 60% increase in peak metformin plasma and whole blood concentrations and a 40% increase in plasma and whole blood metformin AUC. There was no change in elimination half-life in the single-dose study. Metformin had no effect on cimetidine pharmacokinetics.

In healthy volunteers, the pharmacokinetics of metformin and propranolol, and metformin and ibuprofen were not affected when coadministered in single-dose interaction studies.

Metformin is negligibly bound to plasma proteins and is, therefore, less likely to interact with highly protein-bound drugs such as salicylates, sulfonamides, chloramphenicol, and probenecid, as compared to the sulfonylureas, which are extensively bound to serum proteins.

Other:

Carbonic Anhydrase Inhibitors

Topiramate or other carbonic anhydrase inhibitors (e.g., zonisamide, acetazolamide or dichlorphenamide) frequently causes a decrease in serum bicarbonate and induce non-anion gap, hyperchloremic metabolic acidosis. Concomitant use of these drugs with glipizide and metformin hydrochloride may increase the risk for lactic acidosis. Consider more frequent monitoring of these patients.

Alcohol

Alcohol is known to potentiate the effect of metformin on lactate metabolism. Warn patients against excessive alcohol intake while receiving glipizide and metformin hydrochloride.

Carcinogenesis, Mutagenesis, Impairment of Fertility:

No animal studies have been conducted with the combined products in glipizide and metformin hydrochloride tablets. The following data are based on findings in studies performed with the individual products.

Glipizide:

A 20-month study in rats and an 18-month study in mice at doses up to 75 times the maximum human dose revealed no evidence of drug-related carcinogenicity. Bacterial and in vivomutagenicity tests were uniformly negative. Studies in rats of both sexes at doses up to 75 times the human dose showed no effects on fertility.

Metformin Hydrochloride:

Long-term carcinogenicity studies were performed with metformin alone in rats (dosing duration of 104 weeks) and mice (dosing duration of 91 weeks) at doses up to and including 900 mg/kg/day and 1500 mg/kg/day, respectively. These doses are both approximately 4 times the maximum recommended human daily (MRHD) dose of 2000 mg of the metformin component of glipizide and metformin hydrochloride tablets based on body surface area comparisons. No evidence of carcinogenicity with metformin alone was found in either male or female mice. Similarly, there was no tumorigenic potential observed with metformin alone in male rats. There was, however, an increased incidence of benign stromal uterine polyps in female rats treated with 900 mg/kg/day of metformin alone.

There was no evidence of a mutagenic potential of metformin alone in the following in vitrotests: Ames test (S. typhimurium), gene mutation test (mouse lymphoma cells), or chromosomal aberrations test (human lymphocytes). Results in the in vivomouse micronucleus test were also negative.

Fertility of male or female rats was unaffected by metformin alone when administered at doses as high as 600 mg/kg/day, which is approximately three times the maximum recommended human daily dose of the metformin component of glipizide and metformin hydrochloride tablets based on body surface area comparisons.

Teratogenic Effects: Pregnancy Category C:

Recent information strongly suggests that abnormal blood glucose levels during pregnancy are associated with a higher incidence of congenital abnormalities. Most experts recommend that insulin be used during pregnancy to maintain blood glucose as close to normal as possible. Because animal reproduction studies are not always predictive of human response, glipizide and metformin hydrochloride tablets should not be used during pregnancy unless clearly needed (see below).

There are no adequate and well-controlled studies in pregnant women with glipizide and metformin hydrochloride tablets or its individual components. No animal studies have been conducted with the combined products in glipizide and metformin hydrochloride tablets. The following data are based on findings in studies performed with the individual products.

Glipizide:

Glipizide was found to be mildly fetotoxic in rat reproductive studies at all dose levels (5 to 50 mg/kg). This fetotoxicity has been similarly noted with other sulfonylureas, such as tolbutamide and tolazamide. The effect is perinatal and believed to be directly related to the pharmacologic (hypoglycemic) action of glipizide. In studies in rats and rabbits, no teratogenic effects were found.

Metformin Hydrochloride:

Metformin alone was not teratogenic in rats or rabbits at doses up to 600 mg/kg/day. This represents an exposure of about two and six times the maximum recommended human daily dose of 2000 mg of the metformin component of glipizide and metformin hydrochloride tablets based on body surface area comparisons for rats and rabbits, respectively. Determination of fetal concentrations demonstrated a partial placental barrier to metformin.

Nonteratogenic Effects:

Prolonged severe hypoglycemia (4 to 10 days) has been reported in neonates born to mothers who were receiving a sulfonylurea drug at the time of delivery. This has been reported more frequently with the use of agents with prolonged half-lives. It is not recommended that glipizide and metformin hydrochloride tablets be used during pregnancy. However, if it is used, glipizide and metformin hydrochloride tablets should be discontinued at least one month before the expected delivery date (see Pregnancy; Teratogenic Effects: Pregnancy Category C).

Nursing Mothers:

Although it is not known whether glipizide is excreted in human milk, some sulfonylurea drugs are known to be excreted in human milk. Studies in lactating rats show that metformin is excreted into milk and reaches levels comparable to those in plasma. Similar studies have not been conducted in nursing mothers. Because the potential for hypoglycemia in nursing infants may exist, a decision should be made whether to discontinue nursing or to discontinue glipizide and metformin hydrochloride tablets, taking into account the importance of the drug to the mother. If glipizide and metformin hydrochloride tablets are discontinued, and if diet alone is inadequate for controlling blood glucose, insulin therapy should be considered.

Pediatric Use:

Safety and effectiveness of glipizide and metformin hydrochloride tablets in pediatric patients have not been established.

Geriatric Use:

Of the 345 patients who received glipizide and metformin hydrochloride tablets 2.5 mg/250 mg and 2.5 mg/500 mg in the initial therapy trial, 67 (19.4%) were aged 65 and older while 5 (1.4%) were aged 75 and older. Of the 87 patients who received glipizide and metformin hydrochloride tablets in the second-line therapy trial, 17 (19.5%) were aged 65 and older while one (1.1%) was at least aged 75. No overall differences in effectiveness or safety were observed between these patients and younger patients in either the initial therapy trial or the second-line therapy trial, and other reported clinical experience has not identified differences in response between the elderly and younger patients, but greater sensitivity of some older individuals cannot be ruled out.

In general, dose selection for an elderly patient should be cautious, usually starting at the low end of the dosing range, reflecting the greater frequency of decreased hepatic, renal, or cardiac function, and of concomitant disease or other drug therapy and the higher risk of lactic acidosis. Assess renal function more frequently in elderly patients (see also WARNINGS, PRECAUTIONand DOSAGE AND ADMINISTRATION).

ADVERSE REACTIONS

Glipizide and Metformin Hydrochloride Tablets:

In a double-blind 24-week clinical trial involving glipizide and metformin hydrochloride tablets as initial therapy, a total of 172 patients received glipizide and metformin hydrochloride tablets, 2.5 mg/250 mg, 173 received glipizide and metformin hydrochloride tablets, 2.5 mg/500 mg, 170 received glipizide, and 177 received metformin. The most common clinical adverse events in these treatment groups are listed in Table 4.

Table 4 Clinical Adverse Events >5% in any Treatment Group, by Primary Term, in Initial Therapy Study
Adverse Event | Number (%) of Patients
 | Glipizide Tablets 5 mg N=170 | Metformin Tablets 500 mg N=177 | Glipizide and Metformin Hydrochloride Tablets 2.5 mg/250 mg N=172 | Glipizide and Metformin Hydrochloride Tablets 2.5 mg/500 mg N=173
Upper respiratory infection | 12 (7.1) | 15 (8.5) | 17 (9.9) | 14 (8.1)
Diarrhea | 8 (4.7) | 15 (8.5) | 4 (2.3) | 9 (5.2)
Dizziness | 9 (5.3) | 2 (1.1) | 3 (1.7) | 9 (5.2)
Hypertension | 17 (10.0) | 10 (5.6) | 5 (2.9) | 6 (3.5)
Nausea/vomiting | 6 (3.5) | 9 (5.1) | 1 (0.6) | 3 (1.7)

In a double-blind 18-week clinical trial involving glipizide and metformin hydrochloride tablets as second-line therapy, a total of 87 patients received glipizide and metformin hydrochloride tablets, 84 received glipizide, and 75 received metformin. The most common clinical adverse events in this clinical trial are listed in Table 5.

Table 5 Clinical Adverse Events >5% in any Treatment Group, by Primary Term, in Second-Line Therapy Study
Adverse Event | Number (%) of Patients
 | Glipizide Tablets [The dose of glipizide was fixed at 30 mg daily; doses of metformin andglipizide and metformin hydrochloride tablets were titrated.] 5 mg N=84 | Metformin Tablets 500 mg N=75 | Glipizide and Metformin Hydrochloride Tablets 5 mg/500 mg N=87
Diarrhea | 11 (13.1) | 13 (17.3) | 16 (18.4)
Headache | 5 (6.0) | 4 (5.3) | 11 (12.6)
Upper respiratory infection | 11 (13.1) | 8 (10.7) | 9 (10.3)
Musculoskeletal pain | 6 (7.1) | 5 (6.7) | 7 (8.0)
Nausea/vomiting | 5 (6.0) | 6 (8.0) | 7 (8.0)
Abdominal pain | 7 (8.3) | 5 (6.7) | 5 (5.7)
UTI | 4 (4.8) | 6 (8.0) | 1 (1.1)

Hypoglycemia:

In a controlled initial therapy trial of glipizide and metformin hydrochloride tablets, 2.5 mg/250 mg and 2.5 mg/500 mg the numbers of patients with hypoglycemia documented by symptoms (such as dizziness, shakiness, sweating, and hunger) and a fingerstick blood glucose measurement ≤50 mg/dL were 5 (2.9%) for glipizide, 0 (0%) for metformin, 13 (7.6%) for glipizide and metformin hydrochloride tablets, 2.5 mg/250 mg, and 16 (9.3%) for glipizide and metformin hydrochloride tablets, 2.5 mg/500 mg. Among patients taking either glipizide and metformin hydrochloride tablets, 2.5 mg/250 mg or glipizide and metformin hydrochloride tablets, 2.5 mg/500 mg, 9 (2.6%) patients discontinued glipizide and metformin hydrochloride tablets due to hypoglycemic symptoms and one required medical intervention due to hypoglycemia. In a controlled second-line therapy trial of glipizide and metformin hydrochloride tablets, 5 mg/500 mg, the numbers of patients with hypoglycemia documented by symptoms and a fingerstick blood glucose measurement ≤50 mg/dL were 0 (0%) for glipizide, 1 (1.3%) for metformin, and 11 (12.6%) for glipizide and metformin hydrochloride tablets. One (1.1%) patient discontinued glipizide and metformin hydrochloride tablets therapy due to hypoglycemic symptoms and none required medical intervention due to hypoglycemia (see PRECAUTIONS).

Gastrointestinal Reactions:

Among the most common clinical adverse events in the initial therapy trial were diarrhea and nausea/vomiting; the incidences of these events were lower with both glipizide and metformin hydrochloride tablets dosage strengths than with metformin therapy. There were 4 (1.2%) patients in the initial therapy trial who discontinued glipizide and metformin hydrochloride tablets therapy due to GI adverse events. Gastrointestinal symptoms of diarrhea, nausea/vomiting, and abdominal pain were comparable among glipizide and metformin hydrochloride tablets, glipizide and metformin in the second-line therapy trial. There were 4 (4.6%) patients in the second-line therapy trial who discontinued glipizide and metformin hydrochloride tablets therapy due to GI adverse events.

Glipizide

Gastrointestinal Reactions

Cholestatic and hepatocellular forms of liver injury accompanied by jaundice have been reported rarely in association with glipizide; glipizide and metformin hydrochloride tablets should be discontinued if this occurs.

OVERDOSAGE

Glipizide:

Overdosage of sulfonylureas, including glipizide, can produce hypoglycemia. Mild hypoglycemic symptoms, without loss of consciousness or neurological findings, should be treated aggressively with oral glucose and adjustments in drug dosage and/or meal patterns. Close monitoring should continue until the physician is assured that the patient is out of danger. Severe hypoglycemic reactions with coma, seizure, or other neurological impairment occur infrequently, but constitute medical emergencies requiring immediate hospitalization. If hypoglycemic coma is diagnosed or suspected, the patient should be given a rapid intravenous injection of concentrated (50%) glucose solution. This should be followed by a continuous infusion of a more dilute (10%) glucose solution at a rate that will maintain the blood glucose at a level above 100 mg/dL. Patients should be closely monitored for a minimum of 24 to 48 hours, since hypoglycemia may recur after apparent clinical recovery. Clearance of glipizide from plasma would be prolonged in persons with liver disease. Because of the extensive protein binding of glipizide, dialysis is unlikely to be of benefit.

Metformin Hydrochloride:

Overdose of metformin hydrochloride has occurred, including ingestion of amounts greater than 50 grams. Hypoglycemia was reported in approximately 10% of cases, but no causal association with metformin hydrochloride has been established. Lactic acidosis has been reported in approximately 32% of metformin overdose cases (see WARNINGS). Metformin is dialyzable with a clearance of up to 170 mL/min under good hemodynamic conditions. Therefore, hemodialysis may be useful for removal of accumulated drug from patients in whom metformin overdosage is suspected.

DOSAGE AND ADMINISTRATION

General Considerations:

Dosage of glipizide and metformin hydrochloride tablets must be individualized on the basis of both effectiveness and tolerance while not exceeding the maximum recommended daily dose of 20 mg glipizide/2000 mg metformin.Glipizide and metformin hydrochloride tablets should be given with meals and should be initiated at a low dose, with gradual dose escalation as described below, in order to avoid hypoglycemia (largely due to glipizide), to reduce GI side effects (largely due to metformin), and to permit determination of the minimum effective dose for adequate control of blood glucose for the individual patient.

With initial treatment and during dose titration, appropriate blood glucose monitoring should be used to determine the therapeutic response to glipizide and metformin hydrochloride tablets and to identify the minimum effective dose for the patient. Thereafter, HbA1cshould be measured at intervals of approximately 3 months to assess the effectiveness of therapy. The therapeutic goal in all patients with type 2 diabetes is to decrease FPG, PPG, and HbA1cto normal or as near normal as possible. Ideally, the response to therapy should be evaluated using HbA1c(glycosylated hemoglobin), which is a better indicator of long-term glycemic control than FPG alone.

No studies have been performed specifically examining the safety and efficacy of switching to glipizide and metformin hydrochloride tablets therapy in patients taking concomitant glipizide (or other sulfonylurea) plus metformin. Changes in glycemic control may occur in such patients, with either hyperglycemia or hypoglycemia possible. Any change in therapy of type 2 diabetes should be undertaken with care and appropriate monitoring.

When colesevelam is coadministered with glipizide ER, maximum plasma concentration and total exposure to glipizide is reduced. Therefore, glipizide and metformin hydrochloride tablets should be administered at least 4 hours prior to colesevelam.

Glipizide and Metformin Hydrochloride Tablets in Patients with Inadequate Glycemic Control on Diet and Exercise Alone

For patients with type 2 diabetes whose hyperglycemia cannot be satisfactorily managed with diet and exercise alone, the recommended starting dose of glipizide and metformin hydrochloride tablets is 2.5 mg/250 mg once a day with a meal. For patients whose FPG is 280 mg/dL to 320 mg/dL a starting dose of glipizide and metformin hydrochloride tablets 2.5 mg/500 mg twice daily should be considered. The efficacy of glipizide and metformin hydrochloride tablets in patients whose FPG exceeds 320 mg/dL has not been established. Dosage increases to achieve adequate glycemic control should be made in increments of one tablet per day every two weeks up to maximum of 10 mg/1000 mg or 10 mg/2000 mg glipizide and metformin hydrochloride tablets per day given in divided doses. In clinical trials of glipizide and metformin hydrochloride tablets as initial therapy, there was no experience with total daily doses greater than 10 mg/2000 mg per day.

Glipizide and Metformin Hydrochloride Tablets in Patients with Inadequate Glycemic Control on a Sulfonylurea and/or Metformin

For patients not adequately controlled on either glipizide (or another sulfonylurea) or metformin alone, the recommended starting dose of glipizide and metformin hydrochloride tablets is 2.5 mg/500 mg or 5 mg/500 mg twice daily with the morning and evening meals. In order to avoid hypoglycemia, the starting dose of glipizide and metformin hydrochloride tablets should not exceed the daily doses of glipizide or metformin already being taken. The daily dose should be titrated in increments of no more than 5 mg/500 mg up to the minimum effective dose to achieve adequate control of blood glucose or to a maximum dose of 20 mg/2000 mg per day.

Patients previously treated with combination therapy of glipizide (or another sulfonylurea) plus metformin may be switched to glipizide and metformin hydrochloride tablets 2.5 mg/500 mg or 5 mg/500 mg; the starting dose should not exceed the daily dose of glipizide (or equivalent dose of another sulfonylurea) and metformin already being taken. The decision to switch to the nearest equivalent dose or to titrate should be based on clinical judgment. Patients should be monitored closely for signs and symptoms of hypoglycemia following such a switch and the dose of glipizide and metformin hydrochloride tablets should be titrated as described above to achieve adequate control of blood glucose.

Recommendations for Use in Renal Impairment

Assess renal function prior to initiation of glipizide and metformin hydrochloride and periodically thereafter.

Glipizide and metformin hydrochloride is contraindicated in patients with an estimated glomerular filtration rate (eGFR) below 30 mL/minute/1.73 m^2.

Initiation of glipizide and metformin hydrochloride in patients with an eGFR between 30 – 45 mL/minute/1.73 m^2is not recommended.

In patients taking glipizide and metformin hydrochloride whose eGFR later falls below 45 mL/min/1.73 m^2, assess the benefit risk of continuing therapy.

Discontinue glipizide and metformin hydrochloride if the patient's eGFR later falls below 30 mL/minute/1.73 m^2. (See WARNINGS.)

Discontinuation for Iodinated Contrast Imaging Procedures

Discontinue glipizide and metformin hydrochloride at the time of, or prior to, an iodinated contrast imaging procedure in patients with an eGFR between 30 and 60 mL/min/1.73 m^2; in patients with a history of liver disease, alcoholism or heart failure; or in patients who will be administered intra-arterial iodinated contrast. Re-evaluate eGFR 48 hours after the imaging procedure; restart glipizide and metformin hydrochloride if renal function is stable.

Specific Patient Populations:

Glipizide and metformin hydrochloride tablets are not recommended for use during pregnancy or for use in pediatric patients. The initial and maintenance dosing of glipizide and metformin hydrochloride tablets should be conservative in patients with advanced age, due to the potential for decreased renal function in this population. Any dosage adjustment requires a careful assessment of renal function. Generally, elderly, debilitated, and malnourished patients should not be titrated to the maximum dose of glipizide and metformin hydrochloride tablets to avoid the risk of hypoglycemia. Monitoring of renal function is necessary to aid in prevention of metformin-associated lactic acidosis, particularly in the elderly (see WARNINGS and PRECAUTIONS).

HOW SUPPLIED

Glipizide and Metformin Hydrochloride Tablets, 5 mg/500 mg are pink-colored, biconvex, modified capsule-shaped, film-coated tablet, debossed with "ZE66" on one side and plain on other side and are supplied as follows:

NDC: 70518-0908-00

NDC: 70518-0908-01

PACKAGING: 180 in 1 BOTTLE PLASTIC

PACKAGING: 90 in 1 BOTTLE PLASTIC

Store at 20°C to 25° C (68°F to 77° F) [See USP Controlled Room Temperature].

Dispense in a tight container.

Repackaged and Distributed By:

Remedy Repack, Inc.

625 Kolter Dr. Suite #4 Indiana, PA 1-724-465-8762

STORAGE AND HANDLING

Store at 20°C to 25° C (68°F to 77° F) [See USP Controlled Room Temperature].

Dispense in a tight container.

Patient Information Leaflet

Glipizide and Metformin Hydrochloride

((glip'-i-zide and met-for'-min hye"-dro-klor'-ide))

Tablets, USP

WARNING:

A small number of people who have taken metformin hydrochloride have developed a serious condition called lactic acidosis. Tell your doctor if you have severe kidney problems. (see Question Nos. 9 to 12).

Q1. Why do I need to take Glipizide and Metformin Hydrochloride Tablets?

Your doctor has prescribed glipizide and metformin hydrochloride tablets to treat your type 2 diabetes. This is also known as non-insulin-dependent diabetes mellitus.

Q2. What is type 2 diabetes?

People with diabetes are not able to make enough insulin and/or respond normally to the insulin their body does make. When this happens, sugar (glucose) builds up in the blood. This can lead to serious medical problems including kidney damage, amputations, and blindness. Diabetes is also closely linked to heart disease. The main goal of treating diabetes is to lower your blood sugar to a normal level.

Q3. Why is it important to control type 2 diabetes?

The main goal of treating diabetes is to lower your blood sugar to a normal level. Studies have shown that good control of blood sugar may prevent or delay complications such as heart disease, kidney disease, or blindness.

Q4. How is type 2 diabetes usually controlled?

High blood sugar can be lowered by diet and exercise, by a number of oral medications, and by insulin injections. Before taking glipizide and metformin hydrochloride tablets you should first try to control your diabetes by exercise and weight loss. Even if you are taking glipizide and metformin hydrochloride tablets, you should still exercise and follow the diet recommended for your diabetes.

Q5. Does Glipizide and Metformin Hydrochloride Tablet work differently from other glucose-control medications?

Yes it does. Glipizide and metformin hydrochloride tablet combines two glucose lowering drugs, glipizide and metformin. These two drugs work together to improve the different metabolic defects found in type 2 diabetes. Glipizide lowers blood sugar primarily by causing more of the body's own insulin to be released, and metformin lowers blood sugar, in part, by helping your body use your own insulin more effectively. Together, they are efficient in helping you achieve better glucose control.

Q6. What happens if my blood sugar is still too high?

When blood sugar cannot be lowered enough by glipizide and metformin hydrochloride tablets, your doctor may prescribe injectable insulin or take other measures to control your diabetes.

Q7. Can Glipizide and Metformin Hydrochloride Tablets cause side effects?

Glipizide and metformin hydrochloride tablets, like all blood sugar-lowering medications, can cause side effects in some patients. Most of these side effects are minor. However, there are also serious, but rare, side effects related to glipizide and metformin hydrochloride tablets (see Question Nos. 9-13).

Q8. What are the most common side effects of Glipizide and Metformin Hydrochloride Tablets?

The most common side effects of glipizide and metformin hydrochloride tablets are normally minor ones such as diarrhea, nausea, and upset stomach. If these side effects occur, they usually occur during the first few weeks of therapy. Taking your glipizide and metformin hydrochloride tablets with meals can help reduce these side effects.

Symptoms of hypoglycemia (low blood sugar), such as lightheadedness, dizziness, shakiness, or hunger may occur. The risk of hypoglycemic symptoms increases when meals are skipped, too much alcohol is consumed, or heavy exercise occurs without enough food. Following the advice of your doctor can help you to avoid these symptoms.

Q9. Are there any serious side effects that Glipizide and Metformin Hydrochloride Tablets can cause?

People who have a condition known as glucose-6-phosphate dehydrogenase (G6PD) deficiency and who take glipizide and metformin hydrochloride may develop hemolytic anemia (fast breakdown of red blood cells). G6PD deficiency usually runs in families. Tell your doctor if you or any members of your family have been diagnosed with G6PD deficiency before you start taking Glipizide and metformin hydrochloride tablets.

Glipizide and metformin hydrochloride tablets rarely cause serious side effects. Metformin, one of the medicines in glipizide and metformin hydrochloride can cause a rare but serious condition called lactic acidosis (a buildup of an acid in the blood) that can cause death. Lactic acidosis is a medical emergency and must be treated in the hospital.

Call your doctor right away if you have any of the following symptoms, which could be

signs of lactic acidosis:

- you feel cold in your hands or feet
- you feel dizzy or lightheaded
- you have a slow or irregular heartbeat
- you feel very weak or tired
- you have unusual (not normal) muscle pain
- you have trouble breathing
- you feel sleepy or drowsy
- you have stomach pains, nausea or vomiting

Most people who have had lactic acidosis with metformin have other things that, combined with the metformin, led to the lactic acidosis. Tell your doctor if you have any of the following, because you have a higher chance for getting lactic acidosis with glipizide and metformin hydrochloride if you:

- have severe kidney problems
- your kidneys are affected by certain x-ray tests that use injectable dye. Tell your doctor if you are going to get an injection or dye or contrast agents for an x-ray procedure.
- have liver problems
- drink alcohol very often, or drink a lot of alcohol in short-term "binge" drinking
- get dehydrated (lose a large amount of body fluids). This can happen if you are sick with a fever, vomiting, or diarrhea. Dehydration can also happen when you sweat a lot with activity or exercise and do not drink enough fluids
- have surgery
- have a heart attack, severe infection, or stroke

The best way to keep from having a problem with lactic acidosis from metformin is to tell your doctor if you have any of the problems in the list above. Your doctor may decide to stop your glipizide and metformin hydrochloride for a while if you have any of these things.

Glipizide and metformin hydrochloride can have other serious side effects. See "What are the possible side effects of glipizide and metformin hydrochloride?"

Q10. Can I take Glipizide and Metformin Hydrochloride Tablets with other medications?

Remind your doctor that you are taking glipizide and metformin hydrochloride tablets when any new drug is prescribed or a change is made in how you take a drug already prescribed.

Glipizide and metformin hydrochloride tablets may interfere with the way some drugs work and some drugs may interfere with the action of glipizide and metformin hydrochloride tablets.

Q11. What if I become pregnant while taking Glipizide and Metformin Hydrochloride Tablets?

Tell your doctor if you plan to become pregnant or have become pregnant. As with other oral glucose-control medications, you should not take glipizide and metformin hydrochloride tablets during pregnancy.

Usually your doctor will prescribe insulin while you are pregnant. As with all medications, you and your doctor should discuss the use of glipizide and metformin hydrochloride tablets if you are nursing a child.

Q12. How do I take Glipizide and Metformin Hydrochloride Tablets?

Your doctor will tell you how many glipizide and metformin hydrochloride tablets to take and how often.

This should also be printed on the label of your prescription. You will probably be started on a low dose of glipizide and metformin hydrochloride tablets and your dosage will be increased gradually until your blood sugar is controlled.

Q13. Where can I get more information about Glipizide and Metformin Hydrochloride Tablets?

This leaflet is a summary of the most important information about glipizide and metformin hydrochloride tablets.

If you have any questions or problems, you should talk to your doctor or other healthcare provider about type 2 diabetes as well as glipizide and metformin hydrochloride tablets and its side effects. There is also a leaflet (package insert) written for health professionals that your pharmacist can let you read.

Call your doctor for medical advice about side effects. You may report side effects to FDA at 1-800-FDA-1088.

Repackaged and Distributed By:

Remedy Repack, Inc.

625 Kolter Dr. Suite #4 Indiana, PA 1-724-465-8762

PACKAGE LABEL

DRUG: Glipizide and Metformin Hydrochloride

GENERIC: Glipizide and Metformin Hydrochloride

DOSAGE: TABLET, FILM COATED

ADMINSTRATION: ORAL

NDC: 70518-0908-0

NDC: 70518-0908-1

COLOR: pink

SHAPE: CAPSULE

SCORE: No score

SIZE: 15 mm

IMPRINT: ZE66

PACKAGING: 180 in 1 BOTTLE, PLASTIC

PACKAGING: 90 in 1 BOTTLE, PLASTIC

ACTIVE INGREDIENT(S):

- METFORMIN HYDROCHLORIDE 500mg in 1
- GLIPIZIDE 5mg in 1

INACTIVE INGREDIENT(S):

- CELLULOSE, MICROCRYSTALLINE
- CROSCARMELLOSE SODIUM
- FERRIC OXIDE RED
- HYPROMELLOSES
- MAGNESIUM STEARATE
- POLYETHYLENE GLYCOL, UNSPECIFIED
- POVIDONE
- TITANIUM DIOXIDE